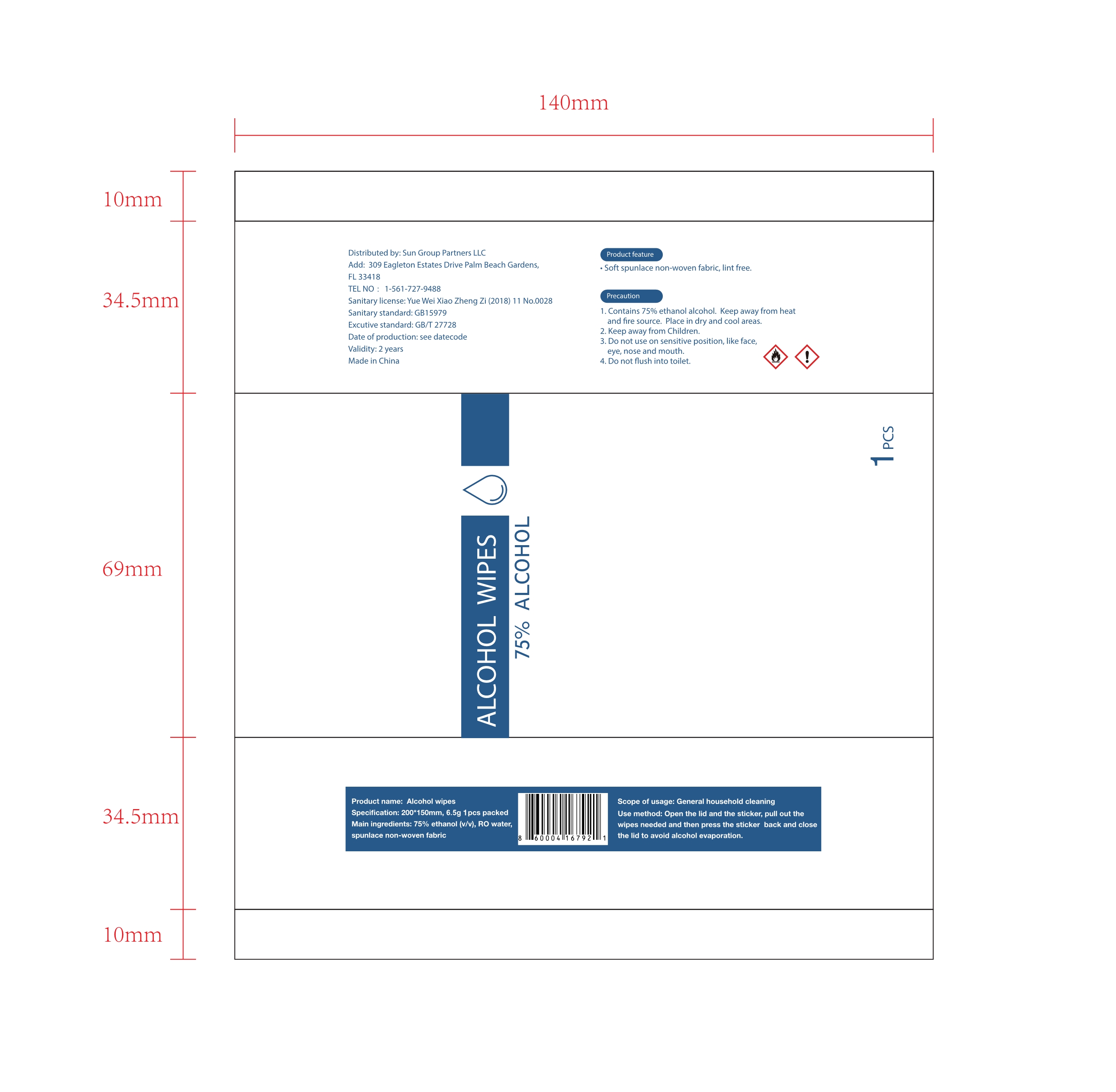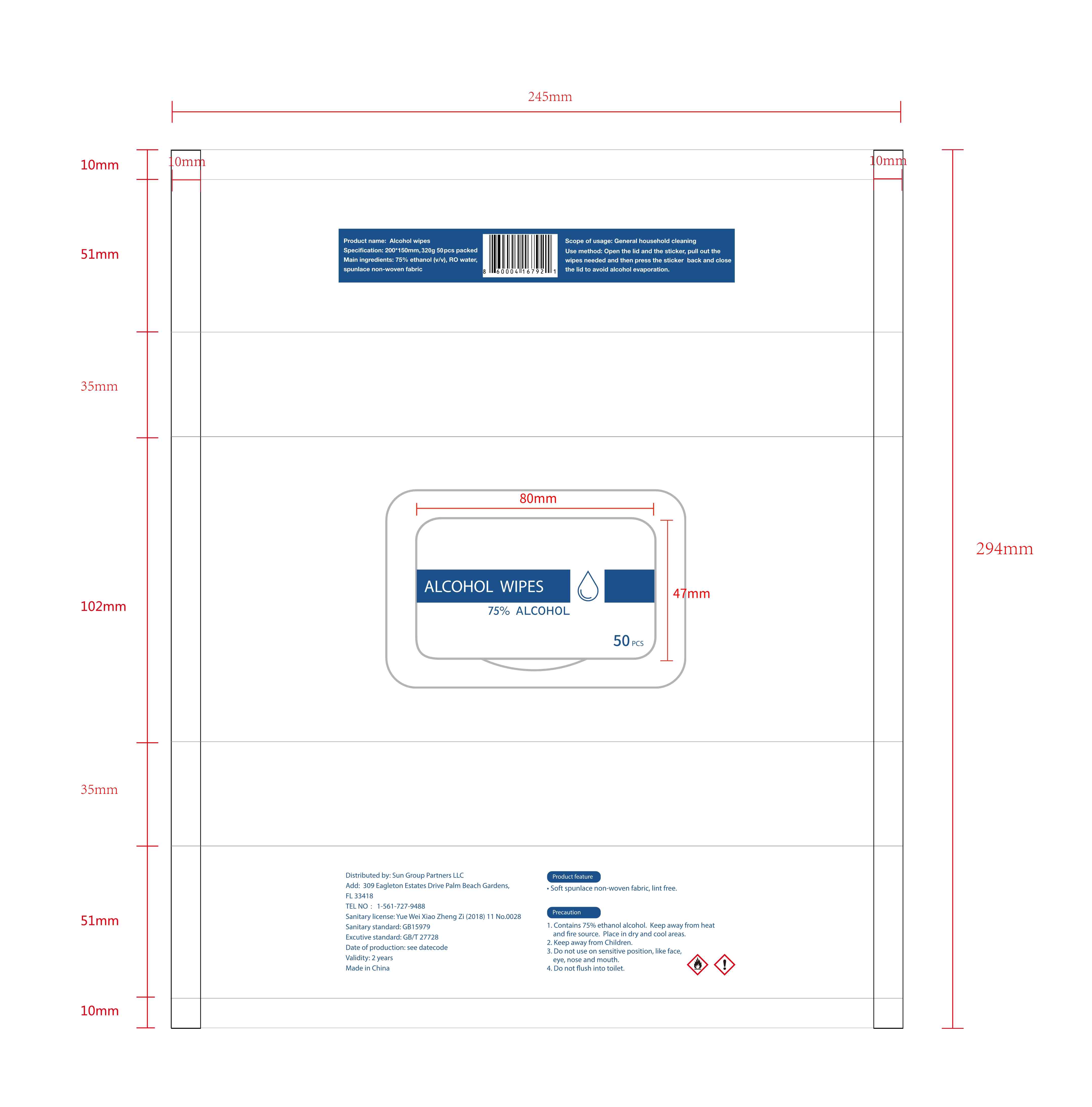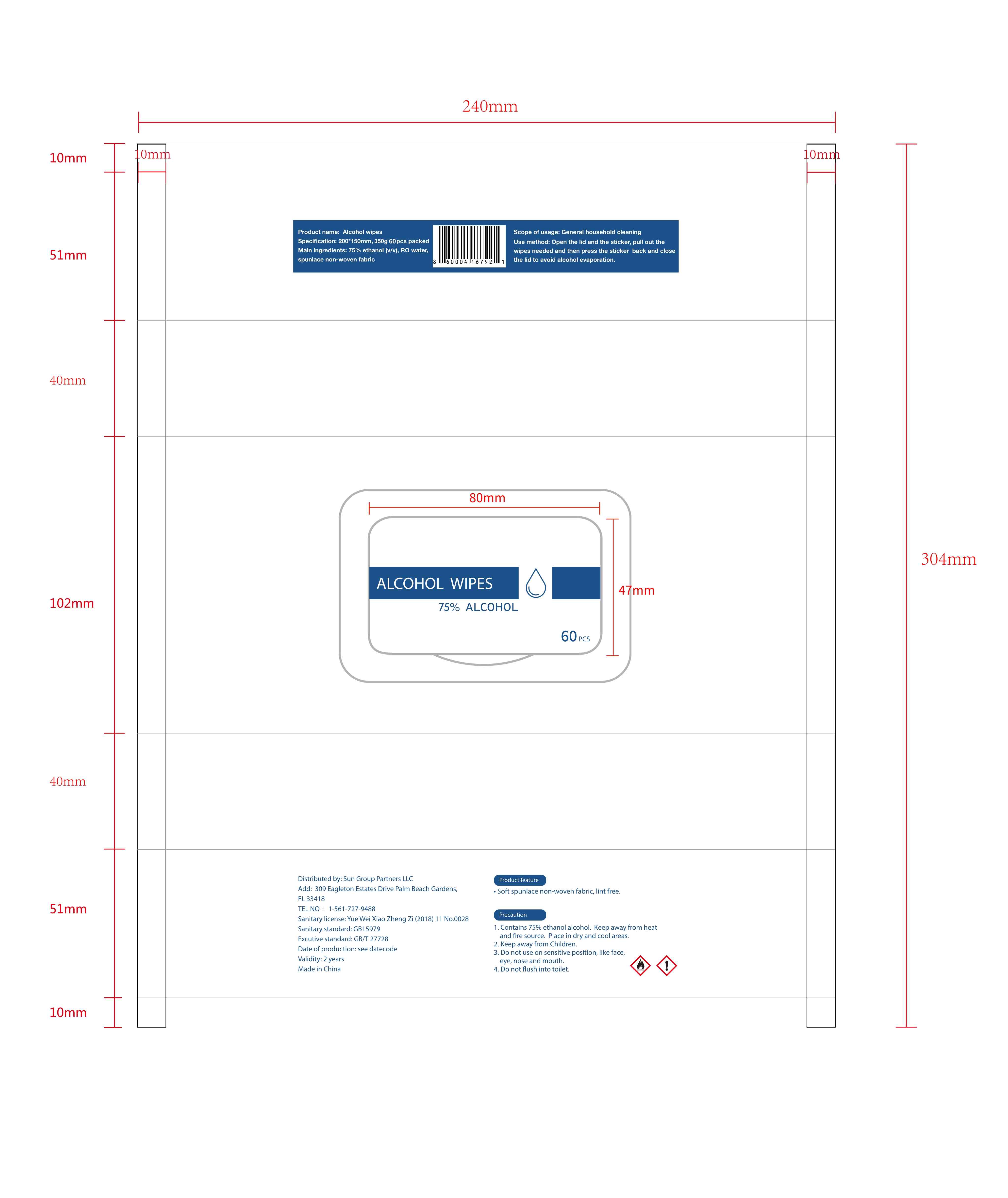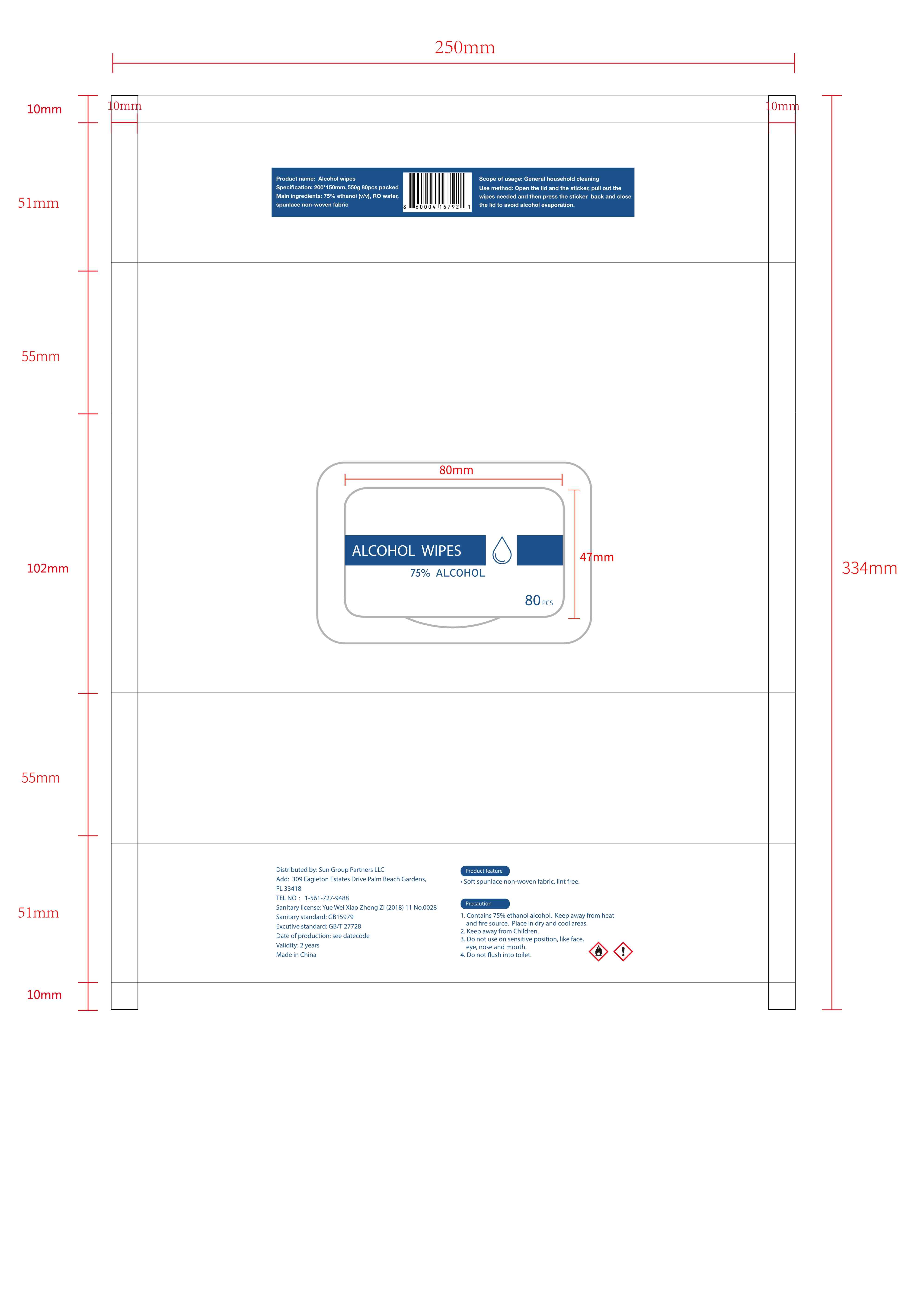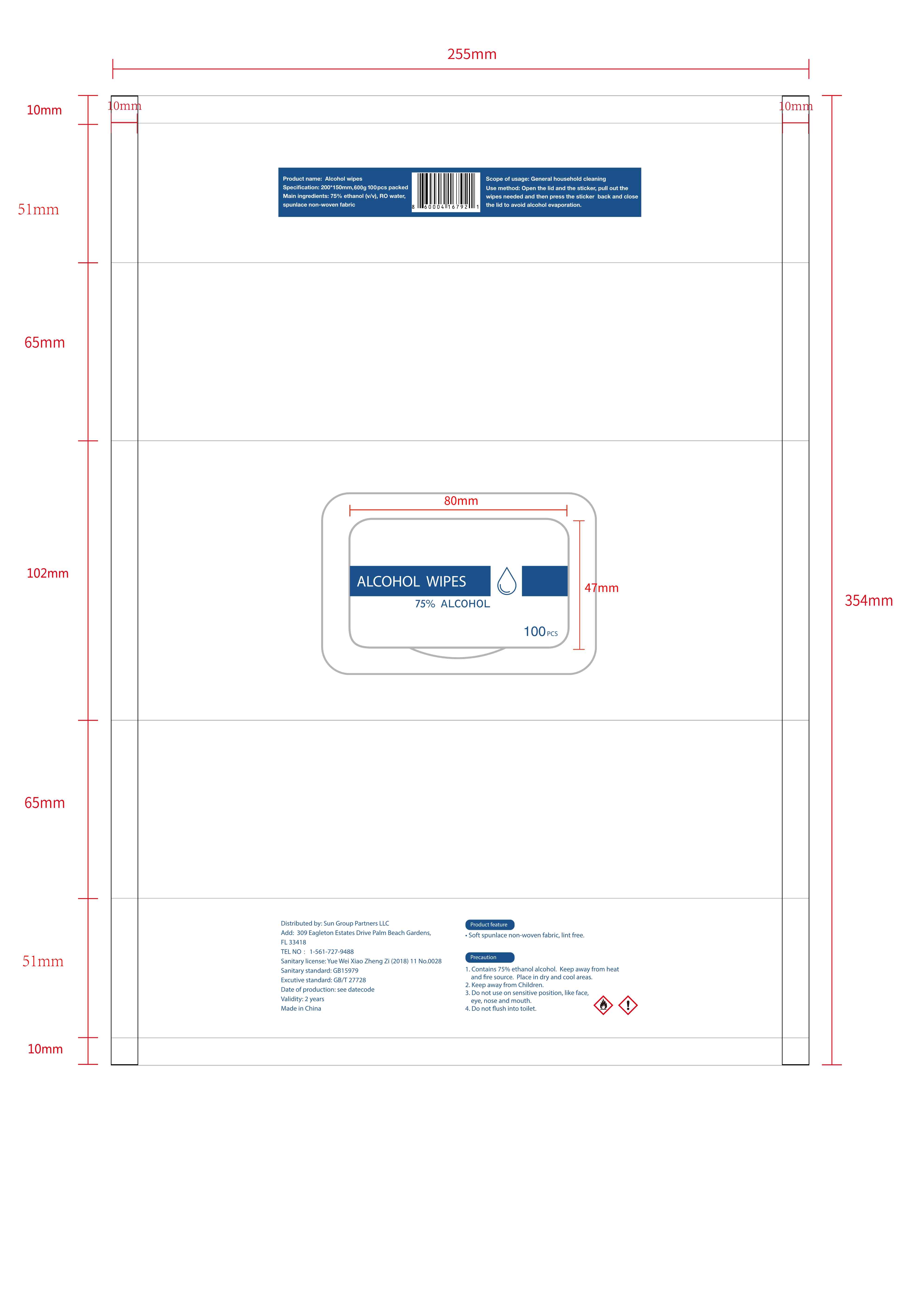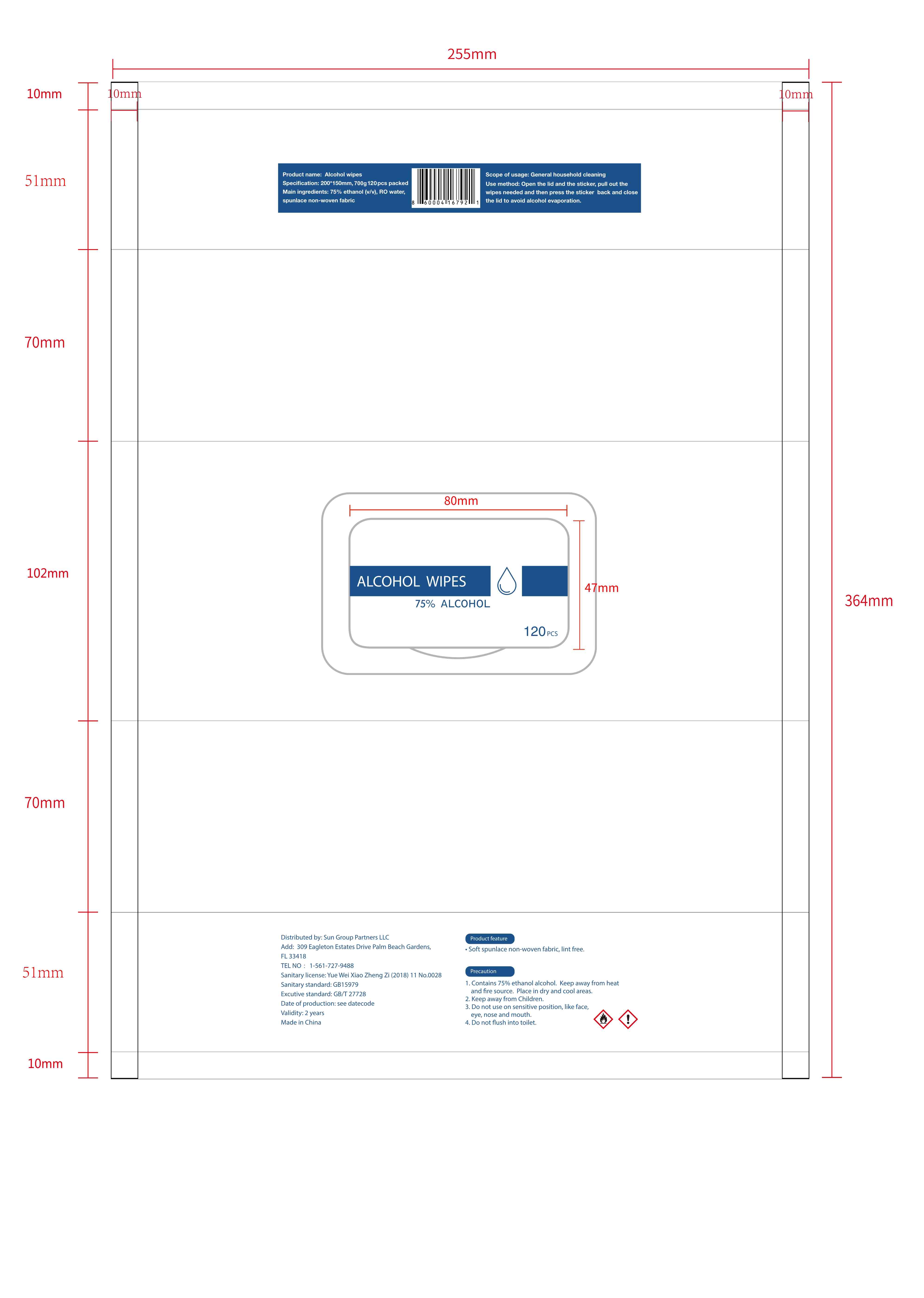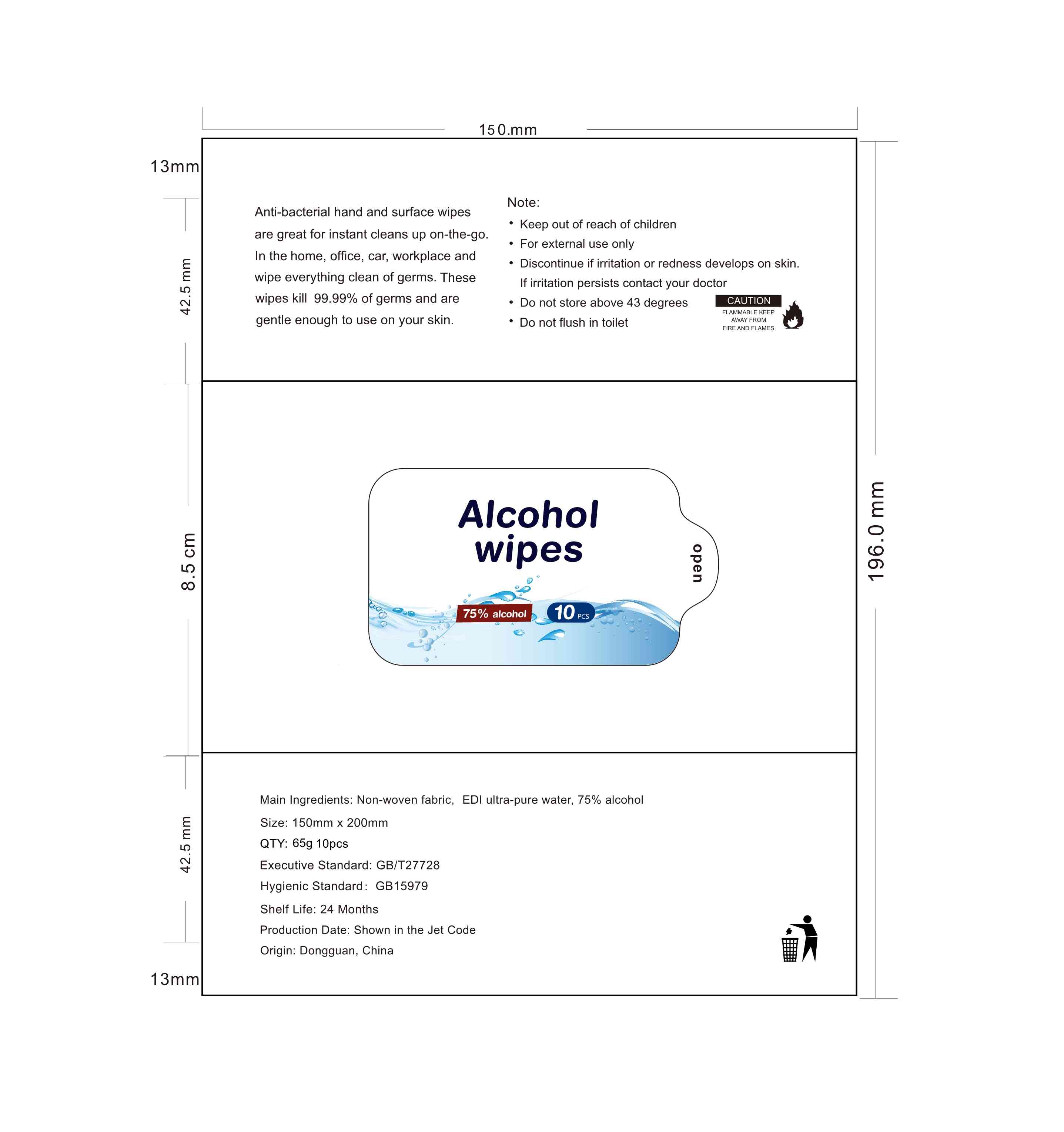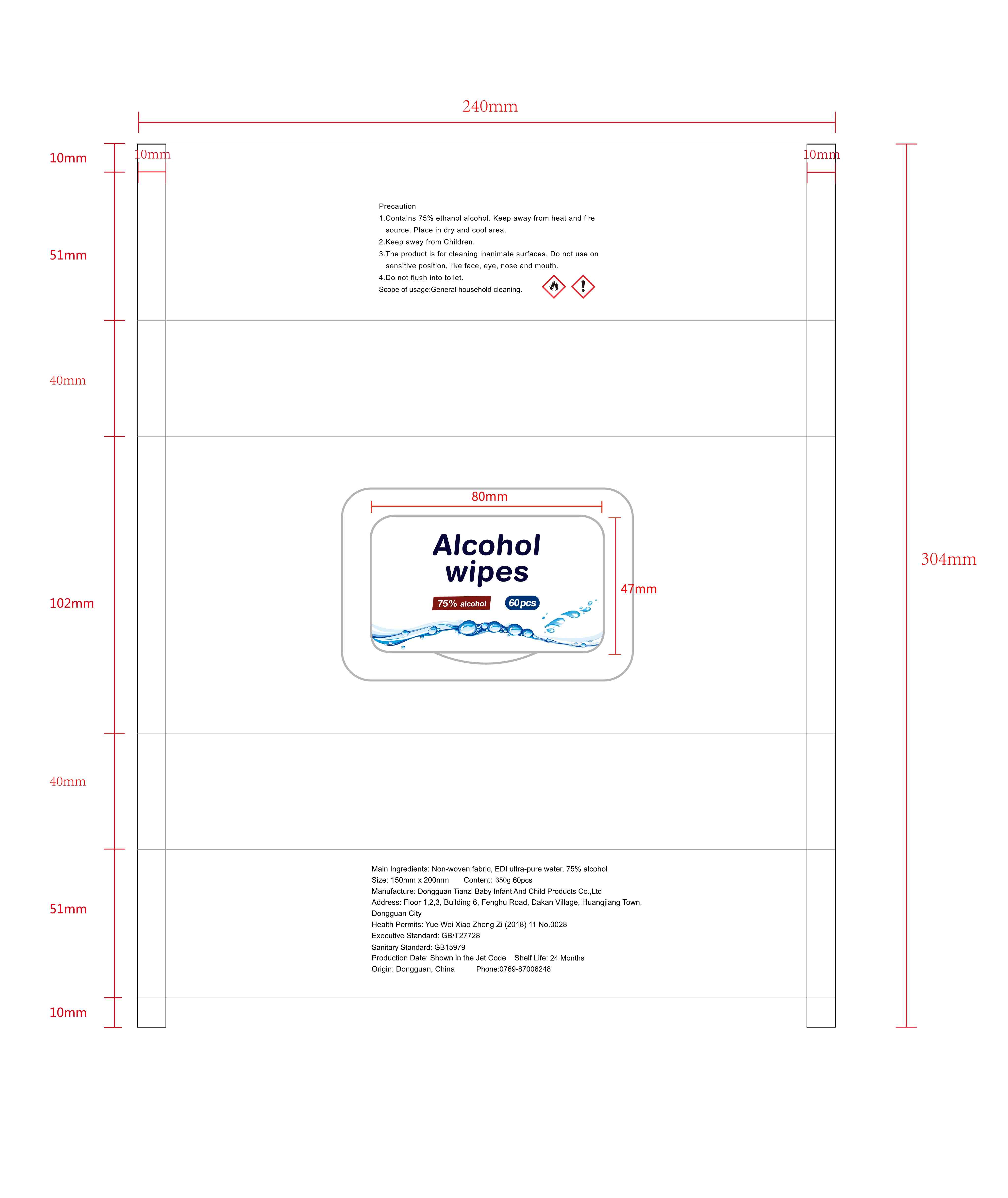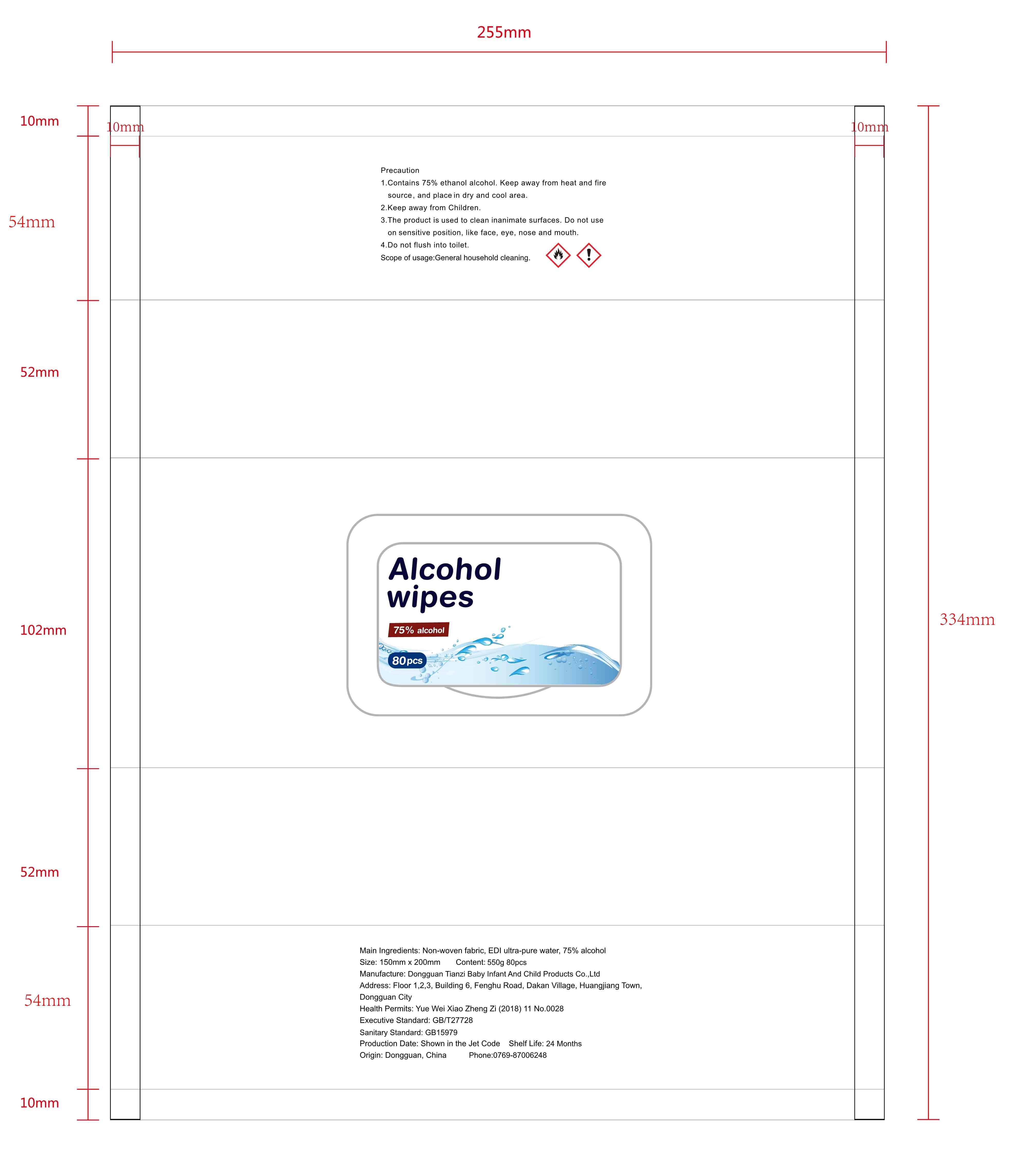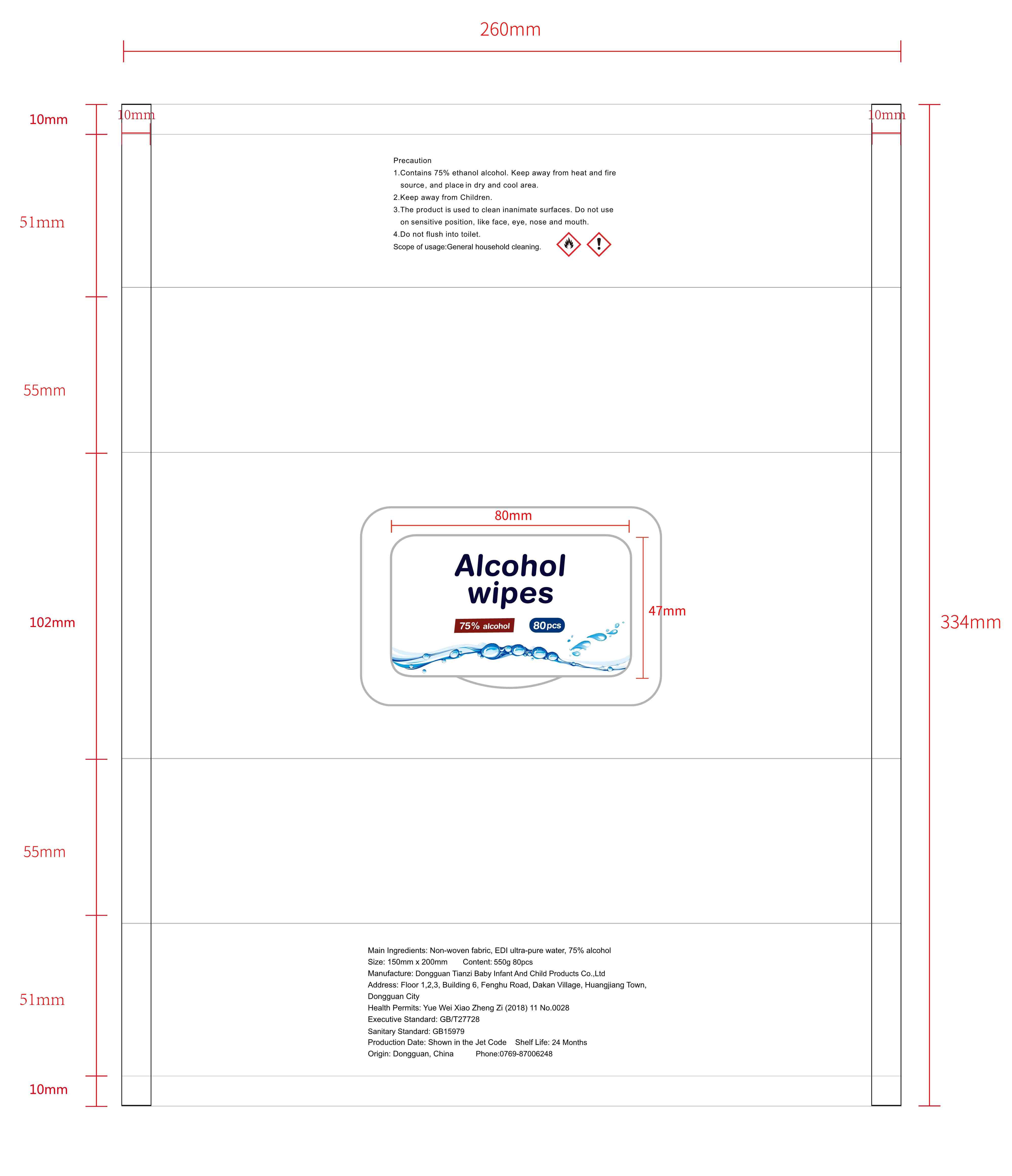 DRUG LABEL: Alcohol wipes 75% alcohol
NDC: 75256-005 | Form: CLOTH
Manufacturer: Dongguan Tianzi Baby Baby Supplies Co., Ltd.
Category: otc | Type: HUMAN OTC DRUG LABEL
Date: 20200729

ACTIVE INGREDIENTS: ALCOHOL 75 mL/100 1
INACTIVE INGREDIENTS: WATER

Alcohol wipes 75% alcohol 75256-005

Main Ingredients

75% alcohol

Purpose

/

INDICATIONS AND USAGE

Open the lid and the sticker, pull out the wipes needed and then press the sticker back and close the lid to avoid alcohol evaporation.

WARNINGS

Contains 75% ethanol alcohol. Keep away from heat and fire source. Place in dry and cool areas

Do not use on sensitive position, like face eye, nose and mouth

WHEN USING

1. Contains 75% ethanol alcohol. Keep away from heat and fire source. Place in dry and cool areas
2. Keep away from Children
3. Do not use on sensitive position, like face eye, nose and mouth
4. Do not flush into toilet

STOP USE

/

Keep away from Children

DOSAGE AND ADMINISTRATION

/

STORAGE AND HANDLING

/

Inactive ingredients

water